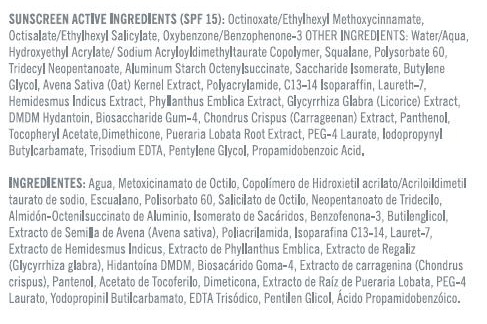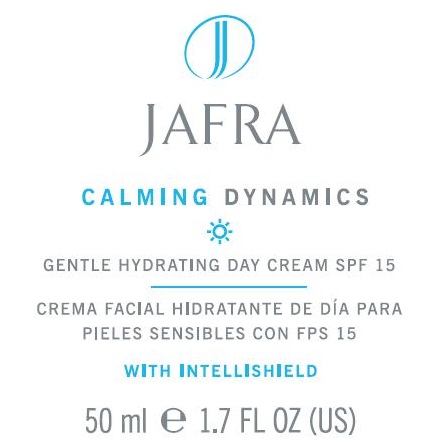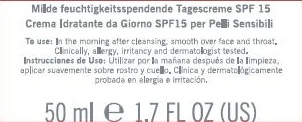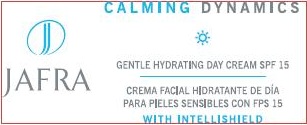 DRUG LABEL: CALM DYNAMICS GENTLE HYDRATING DAY
NDC: 68828-155 | Form: CREAM
Manufacturer: JAFRA COSMETICS INTERNATIONAL
Category: otc | Type: HUMAN OTC DRUG LABEL
Date: 20120531

ACTIVE INGREDIENTS: OCTINOXATE 7 g/100 mL; OCTISALATE 4 g/100 mL; OXYBENZONE 2 g/100 mL
INACTIVE INGREDIENTS: WATER; HYDROXYETHYL ACRYLATE/SODIUM ACRYLOYLDIMETHYL TAURATE COPOLYMER (45000 MPA.S AT 1%); SQUALANE; POLYSORBATE 60; TRIDECYL NEOPENTANOATE; ALUMINUM STARCH OCTENYLSUCCINATE; SACCHARIDE ISOMERATE; OAT; POLYACRYLAMIDE (10000 MW); C13-14 ISOPARAFFIN; LAURETH-7; HEMIDESMUS INDICUS ROOT; BIOSACCHARIDE GUM-1; PHYLLANTHUS EMBLICA FRUIT; GLYCYRRHIZA GLABRA; IODOPROPYNYL BUTYLCARBAMATE; DMDM HYDANTOIN; PUERARIA MONTANA VAR. LOBATA ROOT; CHONDRUS CRISPUS; PANTHENOL; .ALPHA.-TOCOPHEROL ACETATE; PENTYLENE GLYCOL; HYDROXYPHENYL PROPAMIDOBENZOIC ACID; PEG-4 LAURATE

CALM DYNAMICS GENTLE HYDRATING DAY CREAM SPF 15

SUNSCREEN ACTIVE INGREDIENT (SPF 15):
OCTINOXATE/ETHYLHEXYL METHOXYCINNAMATE, OCTISALATE/ETHYLHEXYL SALICYLATE, OXYBENZONE/BENZOPHENONE-3

PURPOSE: SUNSCREEN

INACTIVE INGREDIENT

OTHER INGREDIENTS: WATER/AQUA, HYDROXYETHYL ACRYLATE/SODIUM ACRYLOYLDIMETHYLTAURATE COPOLYMER, SQUALANE, POLYSORBATE 60, TRIDECYL NEOPENTANOATE, ALUMINUM STARCH OCTENYLSUCCINATE, SACCHARIDE ISOMERATE, BUTYLENE GLYCOL, AVENA SATIVA (OAT) KERNEL EXTRACT, POLYACRYLAMIDE, C13-14 ISOPARAFFIN, LURETH-7, HEMIDESMUS INDICUS EXTRACT, PHYLLANTHUS EMBLICA EXTRACT, GLYCYRRHIZA GLABRA (LICORICE) EXTRACT, DMDM HYDANTOIN, BIOSACCHARIDE GUM-4, CHONDRUS CRISPUS (CARRAGEENAN) EXTRACT, PANTHENOL, TOCOPHERYL ACETATE, DIMETHICONE, PUERARIA LOBATA ROOT EXTRACT, PEG-4 LAURATE, IODOPROPYNYL BUTYLCARBAMATE, TRISODIUM EDTA, PENTYLENE GLYCOL, PROPAMIDOBENZOIC ACID.

INDICATIONS AND USAGE

GENTLE HYDRATING DAY CREAM SPF 15

DOSAGE AND ADMINISTRATION

TO USE: IN THE MORNING AFTER CLEANSING, SMOOTH OVER FACE AND THROAT.

WARNINGS

DISCONTINUE USE IF IRRITATION OCCURS.

KEEP OUT OF REACH OF CHILDREN.

PACKAGE LABEL

JAFRA

CALMING DYNAMICS

GENTLE HYDRATING DAY CREAM SPF 15